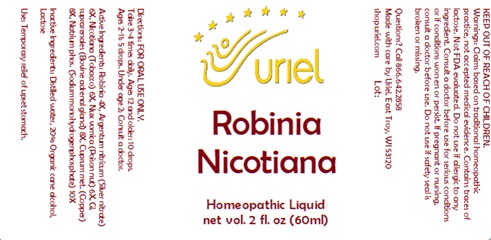 DRUG LABEL: Robinia Nicotiana
NDC: 48951-8397 | Form: LIQUID
Manufacturer: Uriel Pharmacy, Inc.
Category: homeopathic | Type: HUMAN OTC DRUG LABEL
Date: 20231103

ACTIVE INGREDIENTS: TOBACCO LEAF 6 [hp_X]/1 mL; STRYCHNOS NUX-VOMICA SEED 6 [hp_X]/1 mL; BOS TAURUS ADRENAL GLAND 8 [hp_X]/1 mL; COPPER 8 [hp_X]/1 mL; SODIUM PHOSPHATE 10 [hp_X]/1 mL; ROBINIA PSEUDOACACIA BARK 4 [hp_X]/1 mL; SILVER 6 [hp_X]/1 mL
INACTIVE INGREDIENTS: LACTOSE, UNSPECIFIED FORM; WATER; ALCOHOL

Robinia Nicotiana

INDICATIONS AND USAGE

Directions: FOR ORAL USE ONLY.

DOSAGE AND ADMINISTRATION

Take 3-4 times daily. Ages 12 and older: 10 drops. Ages 2-11: 5 drops. Under age 2: Consult a doctor.

ACTIVE INGREDIENT

Active Ingredients: Robinia 4X, Argentum nitricum (Silver nitrate) 6X, Nicotiana (Tobacco) 6X, Nux vomica (Poison nut) 6X, Gl. suprarenales (Bovine adrenal gland)8X, Cuprum met. (Copper) 8X,Natrium phos.(Sodium monohydrogenphosphate) 10X

INACTIVE INGREDIENT

Inactive Ingredients: Distilled water, 20% Organic cane alcohol, Lactose

PURPOSE

Use: Temporary relief of upset stomach.

KEEP OUT OF REACH OF CHILDREN.

WARNINGS

Warnings: Claims based on traditional homeopathic practice, not accepted medical evidence. Contains traces of lactose. Not FDA evaluated. Do not use if allergic to any ingredient. Consult a doctor before use for serious conditions or if conditions worsen or persist. If pregnant or nursing, consult a doctor before use. Do not use if safety seal is broken or missing.

Questions? Call 866.642.2858
Made with care by Uriel, East Troy, WI 53120
shopuriel.com Lot: